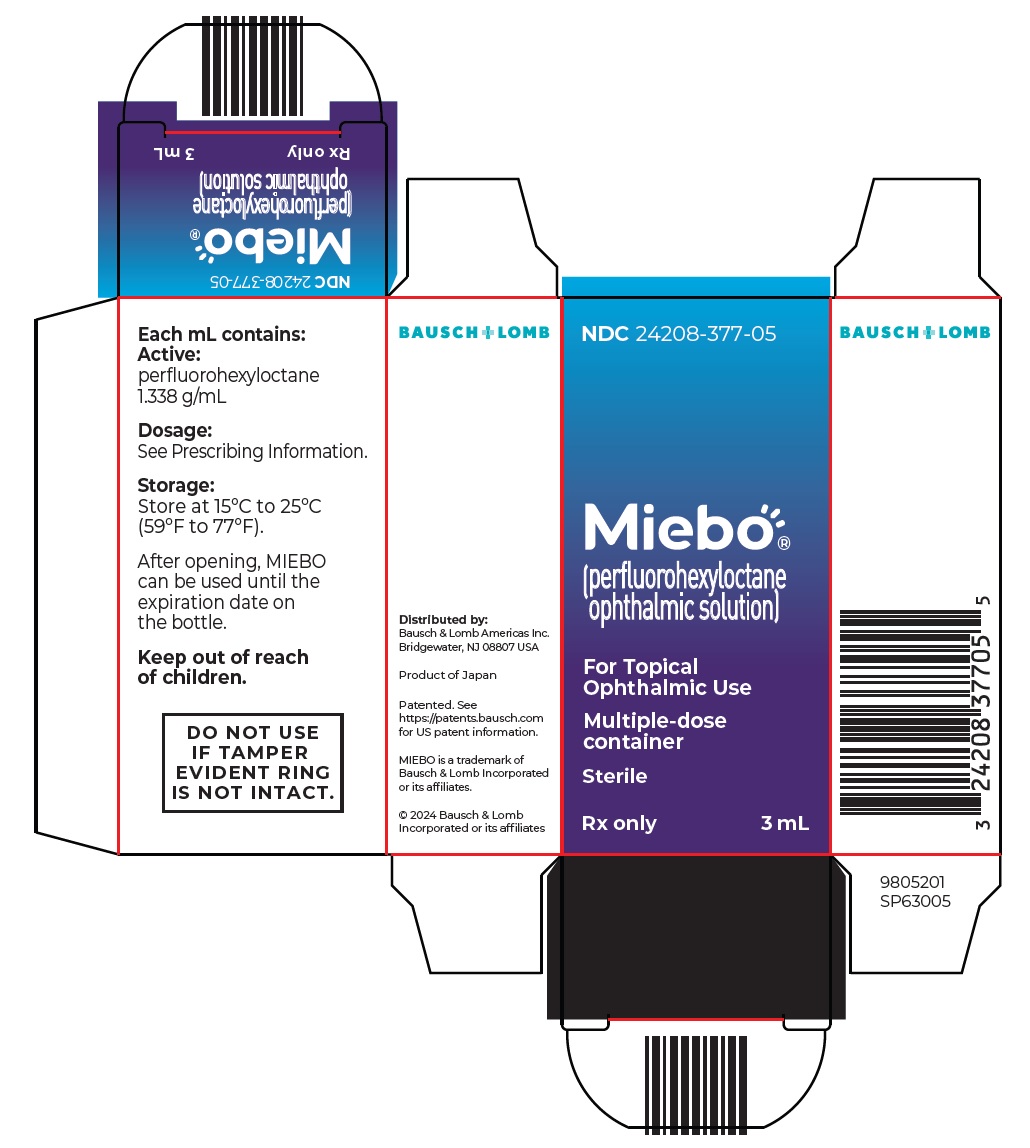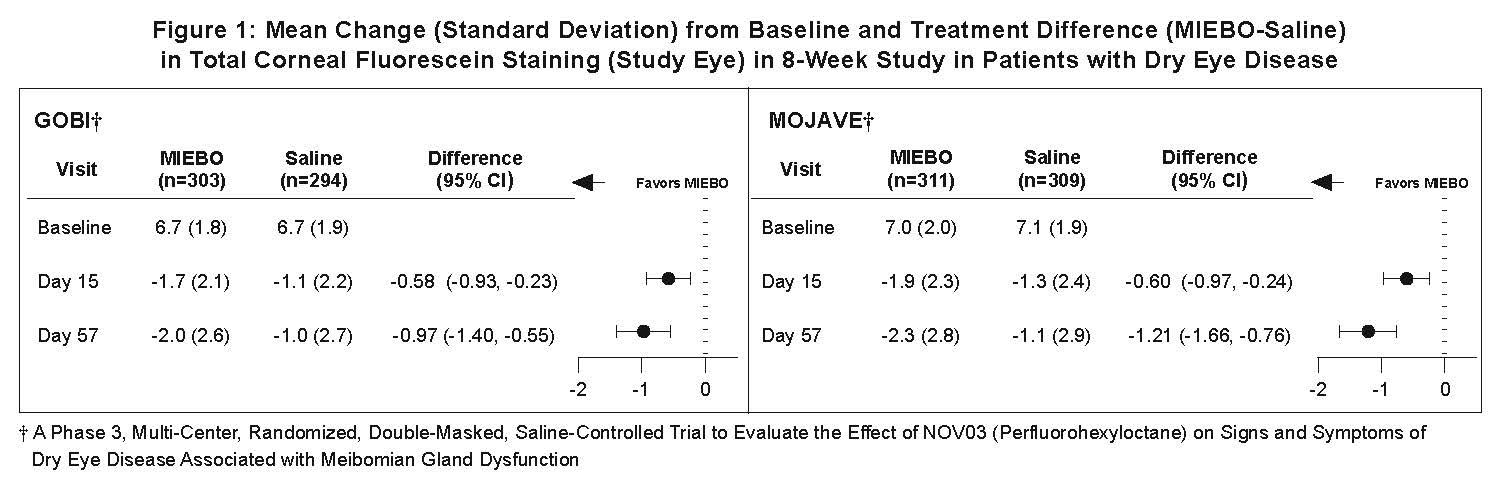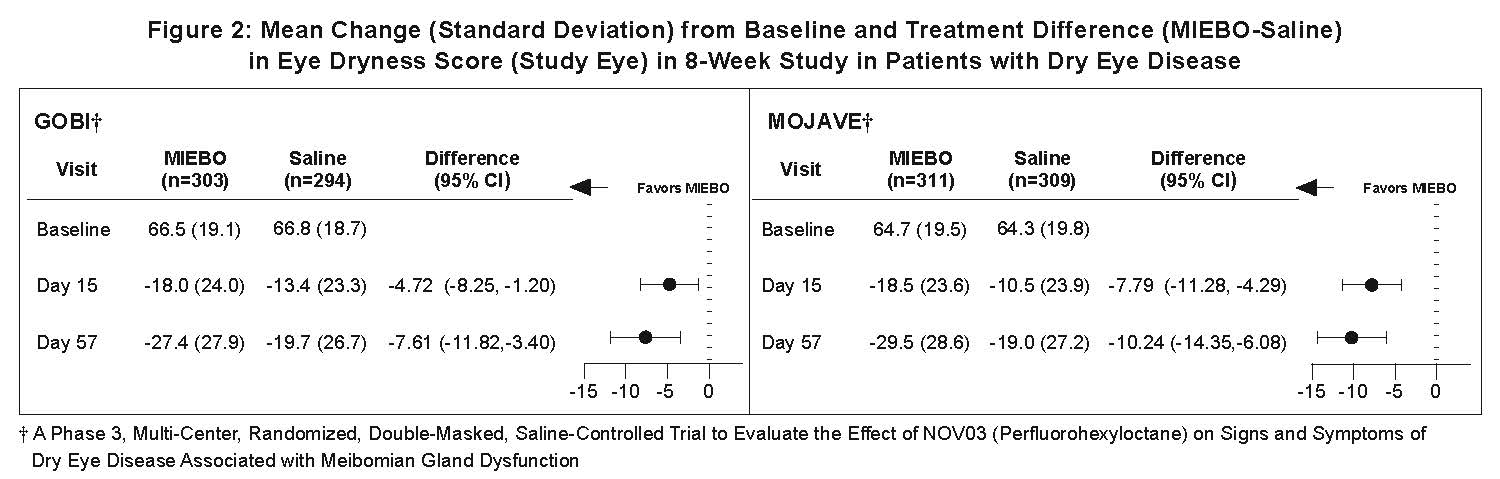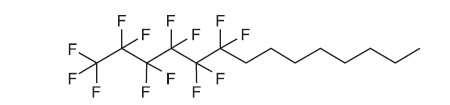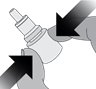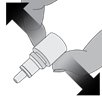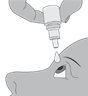 DRUG LABEL: MIEBO
NDC: 24208-377 | Form: SOLUTION
Manufacturer: Bausch & Lomb Incorporated
Category: prescription | Type: HUMAN PRESCRIPTION DRUG LABEL
Date: 20251028

ACTIVE INGREDIENTS: PERFLUOROHEXYLOCTANE 1 mg/1 mg

HIGHLIGHTS OF PRESCRIBING INFORMATION

These highlights do not include all the information needed to use MIEBO safely and effectively. See full prescribing information for MIEBO.
MIEBO®(perfluorohexyloctane ophthalmic solution), for topical ophthalmic use
Initial U.S. Approval: 2023

RECENT MAJOR CHANGES

Contraindications, Hypersensitivity (4.1) 10/2025

1 INDICATIONS AND USAGE

MIEBO (perfluorohexyloctane ophthalmic solution) is a semifluorinated alkane indicated for treatment of the signs and symptoms of dry eye disease. (1)

2 DOSAGE AND ADMINISTRATION

Instill one drop of MIEBO four times daily into each eye. (2.1)

3 DOSAGE FORMS AND STRENGTHS

Ophthalmic solution: 100% perfluorohexyloctane. (3)

4 CONTRAINDICATIONS

Hypersensitivity. (4.1)

6 ADVERSE REACTIONS

Most common ocular adverse reaction was blurred vision. Blurred vision was reported in less than 4% of individuals. (6.1)

To report SUSPECTED ADVERSE REACTIONS, contact Bausch & Lomb Incorporated at 1-800-553-5340 or FDA at 1-800-FDA-1088 or www.fda.gov/medwatch.

FULL PRESCRIBING INFORMATION

1 INDICATIONS AND USAGE

MIEBO®(perfluorohexyloctane ophthalmic solution) is indicated for the treatment of the signs and symptoms of dry eye disease (DED).

2 DOSAGE AND ADMINISTRATION

2.1 Recommended Dosage

Instill one drop of MIEBO four times daily into affected eye(s).

Contact lenses should be removed prior to and for at least 30 minutes after the administration of MIEBO.

2.2 Administration Instructions

Step 1.Remove the cap from eye drop bottle.

Step 2.Holding the bottle upright, gently squeeze the bottle.

Step 3.While squeezing, turn the bottle upside down and release the pressure (drawing air into the bottle).

Step 4.Keeping the bottle upside down, place the bottle above your eye and squeeze it again to release a drop into your eye.

Repeat steps 1 - 4 for the second affected eye.

3 DOSAGE FORMS AND STRENGTHS

MIEBO (perfluorohexyloctane ophthalmic solution) is a sterile, clear and colorless ophthalmic solution containing 100% perfluorohexyloctane.

4 CONTRAINDICATIONS

4.1 Hypersensitivity

MIEBO is contraindicated in patients with a history of hypersensitivity reaction to perfluorohexyloctane [see Adverse Reactions (6.1)] .

5 WARNINGS AND PRECAUTIONS

5.1 Use with Contact Lenses

MIEBO should not be administered while wearing contact lenses. Advise patients that contact lenses should be removed prior to and for at least 30 minutes after administration of MIEBO.

6 ADVERSE REACTIONS

6.1 Clinical Trials Experience

Because clinical trials are conducted under widely varying conditions, adverse reaction rates observed in clinical trials of a drug cannot be directly compared to rates in the clinical trials of another drug and may not reflect the rates observed in practice.

In patients with DED, 614 patients received at least one dose of MIEBO in two randomized controlled clinical trials across 68 sites in the United States. The most common ocular adverse reaction was blurred vision. Blurred vision and conjunctival redness were reported in 1-3% of individuals.

In four premarketing studies (three open-label [n=127], one randomized [n=24 treated with at least one dose of perfluorohexyloctane]) the most common adverse reaction was hypersensitivity.

8 USE IN SPECIFIC POPULATIONS

8.1 Pregnancy

Risk Summary

There are no adequate and well controlled studies with MIEBO in pregnant women.

In animal reproduction studies with oral administration of perfluorohexyloctane during the period of organogenesis, no adverse maternal or developmental effects were observed in rats at doses up to 162 times the recommended human ophthalmic dose (RHOD) (see Data). Maternal toxicity, miscarriages and reduced fetal weights were observed in rabbits at all doses tested, with the lowest dose as 41 times the RHOD.

All pregnancies have a risk of birth defect, loss, or other adverse outcomes. In the US general population, the estimated background risk of major birth defects is 2 to 4%, and of miscarriage is 15 to 20%, of clinically recognized pregnancies.

Data

Animal Data

An embryofetal study was conducted in pregnant rabbits administered perfluorohexyloctane by oral gavage on gestation days 6 to 19, to target the period of organogenesis. Perfluorohexyloctane produced maternal toxicity, characterized by reduced body weight gain and food consumption, and miscarriages at all doses tested, with the lowest dose as ≥ 250 mg/kg/day (41 times the RHOD based on body surface area). Reduced fetal weights were also observed at ≥ 250 mg/kg/day but no fetal mortality or malformations. A no observed adverse effect level (NOAEL) for maternal toxicity was not established in rabbits.

An embryofetal study was conducted in pregnant rats administered perfluorohexyloctane by oral gavage on gestation days 6 to 17, to target the period of organogenesis. There was no evidence of embryofetal toxicity or teratogenicity at doses up to 2,000 mg/kg/day (162 times the RHOD).

8.2 Lactation

There are no data on the presence of perfluorohexyloctane in human milk, the effects on the breastfed infant, or the effects on milk production. The lack of clinical data during lactation precludes a clear determination of the risk of MIEBO to an infant during lactation; however, the developmental and health benefits of breastfeeding should be considered along with the mother’s clinical need for MIEBO.

8.4 Pediatric Use

The safety and effectiveness of MIEBO in pediatric patients below the age of 18 years have not been established.

8.5 Geriatric Use

No overall differences in safety and effectiveness have been observed between elderly and younger patients.

11 DESCRIPTION

MIEBO®(perfluorohexyloctane ophthalmic solution) is a sterile, clear and colorless liquid containing 100% perfluorohexyloctane, for topical ophthalmic use.

The active ingredient is 1,1,1,2,2,3,3,4,4,5,5,6,6-tridecafluorotetradecane and is a semifluorinated alkane. It has a molecular formula of C14H17F13and a molecular weight of 432.26 g/mol. The chemical structure is:

Perfluorohexyloctane is practically immiscible with water. It is miscible with ethanol and most

organic solvents. Each multiple-dose bottle contains 3 mL of perfluorohexyloctane, 1.338 g/mL as a clear and colorless liquid.

12 CLINICAL PHARMACOLOGY

12.1 Mechanism of Action

Perfluorohexyloctane, a semifluorinated alkane, contains 6 perfluorinated carbon atoms and 8 hydrogenated carbon atoms. Perfluorohexyloctane forms a monolayer at the air-liquid interface of the tear film which can be expected to reduce evaporation. The exact mechanism of action for MIEBO in DED is not known.

12.3 Pharmacokinetics

The pharmacokinetics of perfluorohexyloctane following topical ocular administration of MIEBO has not been quantitatively characterized in humans. A single pharmacokinetic (PK) study was conducted that showed low systemic perfluorohexyloctane blood levels after topical ocular administration. Perfluorohexyloctane was not metabolized by human liver microsomes in vitro.

13 NONCLINICAL TOXICOLOGY

13.1 Carcinogenesis, Mutagenesis, Impairment of Fertility

Long-term studies in animals have not been conducted to evaluate the carcinogenic potential of perfluorohexyloctane.

Perfluorohexyloctane was not mutagenic or clastogenic in a standard battery of genotoxicity tests, including a bacterial mutagenicity assay (Ames assay), an in vitro chromosome aberration assay using human peripheral lymphocytes, and an in vivo bone marrow micronucleus assay in rats.

14 CLINICAL STUDIES

In two randomized, multicenter, double-masked, saline-controlled trials (GOBI and MOJAVE), a total of 1,217 patients with a history of DED and clinical signs of meibomian gland dysfunction were randomized to MIEBO or saline 0.6% (1:1 ratio) to evaluate safety and efficacy after receiving MIEBO four times daily (QID) for 57 days.The mean age of the 614 patients who received MIEBO was 57 years (range, 19-87 years). The majority of patients were female (76%).

Effects on Signs of Dry Eye Disease

Total corneal fluorescein staining (tCFS) was recorded at each study visit using a standardized grading system of 0-3 for each of the five areas on the cornea (inferior, superior, central, nasal, and temporal), totaling a maximum tCFS score for each eye of 15. The average baseline tCFS was approximately 6.7 in GOBI and 7.0 in MOJAVE. At Days 15 and 57, a statistically significant reduction in tCFS favoring MIEBO was observed in both studies (Figure 1).

Effects on Symptoms of Dry Eye Disease

Eye dryness score was rated by patients using a visual analogue scale (VAS) (0=no discomfort, 100=maximal discomfort) at each study visit. The baseline VAS eye dryness average score was approximately 67 in GOBI and 65 in MOJAVE. At Days 15 and 57, a statistically significant reduction in VAS eye dryness score favoring MIEBO was observed in both studies (Figure 2).

16 HOW SUPPLIED/STORAGE AND HANDLING

MIEBO®(perfluorohexyloctane ophthalmic solution) is supplied as a sterile, clear and colorless liquid in multiple-dose 5 mL polypropylene bottles with dropper tips and screw caps, packaged in a carton - NDC 24208-377-05.

Storage

Store MIEBO at 15ºC to 25ºC (59ºF to 77ºF). After opening, MIEBO can be used until the expiration date on the bottle.

17 PATIENT COUNSELING INFORMATION

Use with Contact Lenses

Advise patients that contact lenses should be removed prior to and for at least 30 minutes after administration of MIEBO.

Administration Instructions

Advise patients to instill one drop of MIEBO four times daily into each eye as depicted in the Administration Instructions [see Dosage and Administration (2.2)] .

Distributed by:

Bausch & Lomb Americas Inc.

Bridgewater, NJ 08807 USA

Patented. See https://patents.bausch.comfor US patent information.

MIEBO is a trademark of Bausch & Lomb Incorporated or its affiliates.

© 2025 Bausch & Lomb Incorporated or its affiliates

9805301

PACKAGE/LABEL PRINCIPAL DISPLAY PANEL

NDC24208-377-05

Miebo®
(perfluorohexyloctane
ophthalmic solution)

For Topical
Ophthalmic Use

Multiple-dose

container

Sterile

Rx only

3 mL

9805201

SP63005